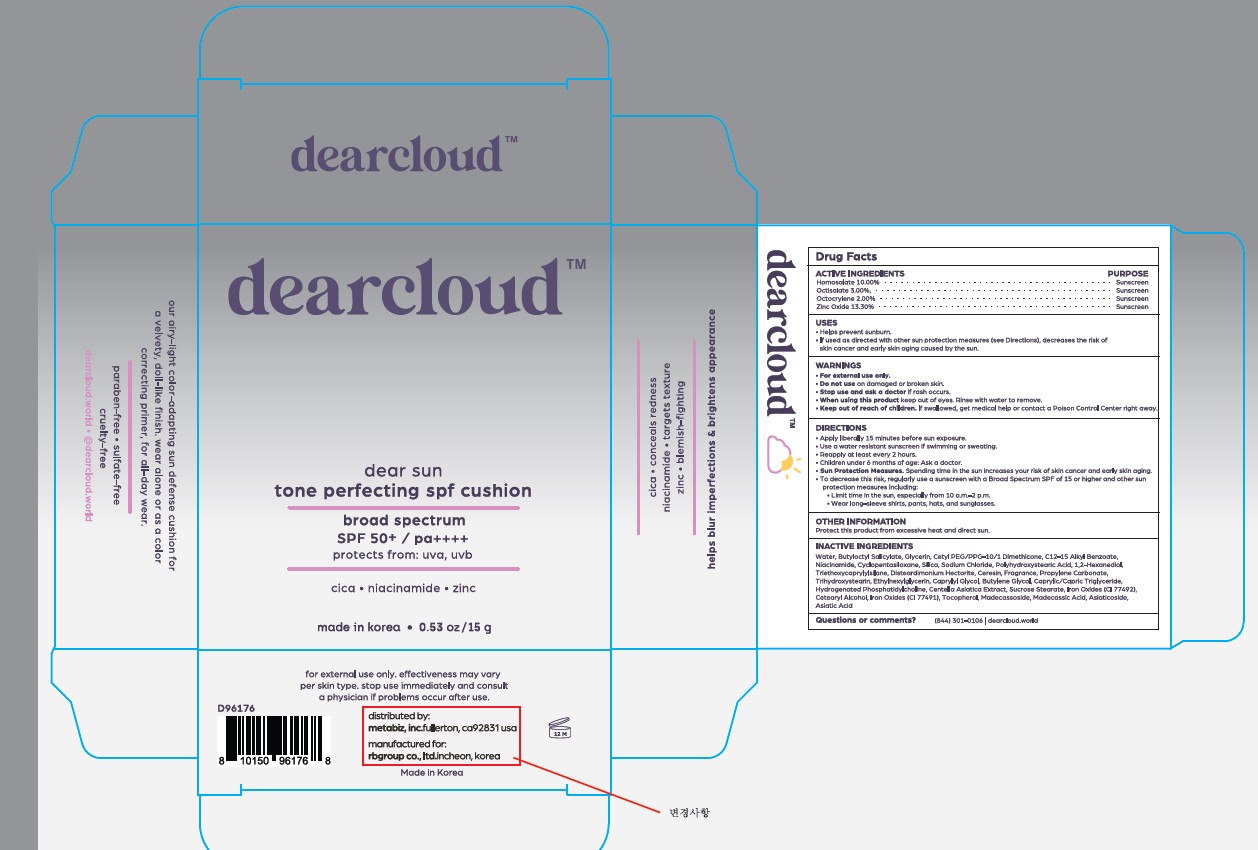 DRUG LABEL: Dear Sun Tone Perfecting SPF Cushion
NDC: 84326-001 | Form: CREAM
Manufacturer: RBGROUP Co., Ltd
Category: otc | Type: HUMAN OTC DRUG LABEL
Date: 20251216

ACTIVE INGREDIENTS: HOMOSALATE 10 g/100 g; OCTISALATE 3 g/100 g; OCTOCRYLENE 2 g/100 g; ZINC OXIDE 13.3 g/100 g
INACTIVE INGREDIENTS: WATER; BUTYLOCTYL SALICYLATE; GLYCERIN; CETYL PEG/PPG-10/1 DIMETHICONE (HLB 4); ALKYL (C12-15) BENZOATE; NIACINAMIDE; CYCLOMETHICONE 5; SILICON DIOXIDE; SODIUM CHLORIDE; POLYHYDROXYSTEARIC ACID (2300 MW); 1,2-HEXANEDIOL; TRIETHOXYCAPRYLYLSILANE; DISTEARDIMONIUM HECTORITE; CERESIN; PROPYLENE CARBONATE; TRIHYDROXYSTEARIN; ETHYLHEXYLGLYCERIN; CAPRYLYL GLYCOL; BUTYLENE GLYCOL; MEDIUM-CHAIN TRIGLYCERIDES; CENTELLA ASIATICA TRITERPENOIDS; SUCROSE STEARATE; FERRIC OXIDE YELLOW; CETOSTEARYL ALCOHOL; FERRIC OXIDE RED; TOCOPHEROL; MADECASSOSIDE; MADECASSIC ACID; ASIATICOSIDE; ASIATIC ACID

84326-001_Dear Sun Tone Perfecting SPF Cushion

ACTIVE INGREDIENT

Homosalate 10.00%

Octisalate 3.00%

Octocrylene 2.00%

Zinc Oxide 13.30%

PURPOSE

Sunscreen

INDICATIONS AND USAGE

Helps prevent sunburn

If used as directed with other sun protection ,easure (see Directions), decreases the risk of skin cancer and early skin aging caused by the sun.

DOSAGE AND ADMINISTRATION

■ apply liberally 15 minutes before sun exposure
■ use a water resistant sunscreen if swimming or sweating.

■ reapply at least every 2 hours.

■ children under 6 months of age: ask a doctor

■ Sun Protection Measures. Spending time in the sun increases your risk of skin cancer and early skin aging.

■ To decrease this risk, regularly use a sunscreen with a Broad Spectrum SPF value of 15 or higher and other sun protection measures including:
– Limit time in the sun, especially from 10 a.m. – 2 p.m.
– Wear long-sleeved shirts, pants, hats and sunglasses

WARNINGS

■ For external use only

■ Do not useon demaged or broken skin.

■ Stop use and ask a doctorif rash occurs.

■ When using this productkeep out of eyes. Rinse with water to remove.

■ Keep out of reach of children.If swallowed, get medical help or contact a Poison Control Center right away.

KEEP OUT OF REACH OF CHILDREN

Keep out of reach of the children. If product is swallowed, get medical help or contact a poison control center right away.

INACTIVE INGREDIENT

Water, Butyloctyl Salicylate, Glycerin, Cetyl PEG/PPG-10/1 Dimethicone, C12-15 Alkyl Benzoate, Niacinamide, Cyclopentasiloxane, Silica, Sodium Chloride, Polyhydroxystearic Acid, 1,2-Hexanediol, Triethoxycaprylylsilane, Disteardimonium Hectorite, Ceresin, Fragrance, Propylene Carbonate, Trihydroxystearin, Ethylhexylglycerin, Caprylyl Glycol, Butylene Glycol, Caprylic/Capric Triglyceride, Hydrogenated Phosphatidylcholine, Centella Asiatica Extract, Sucrose Stearate, Iron Oxides (CI 77492), Cetearyl Alcohol, Iron Oxides (CI 77491), Tocopherol, Madecassoside, Madecassic Acid, Asiaticoside, Asiatic Acid

OTHER SAFETY INFORMATION

Protect the product in this container from excessive heat and direct sunlight